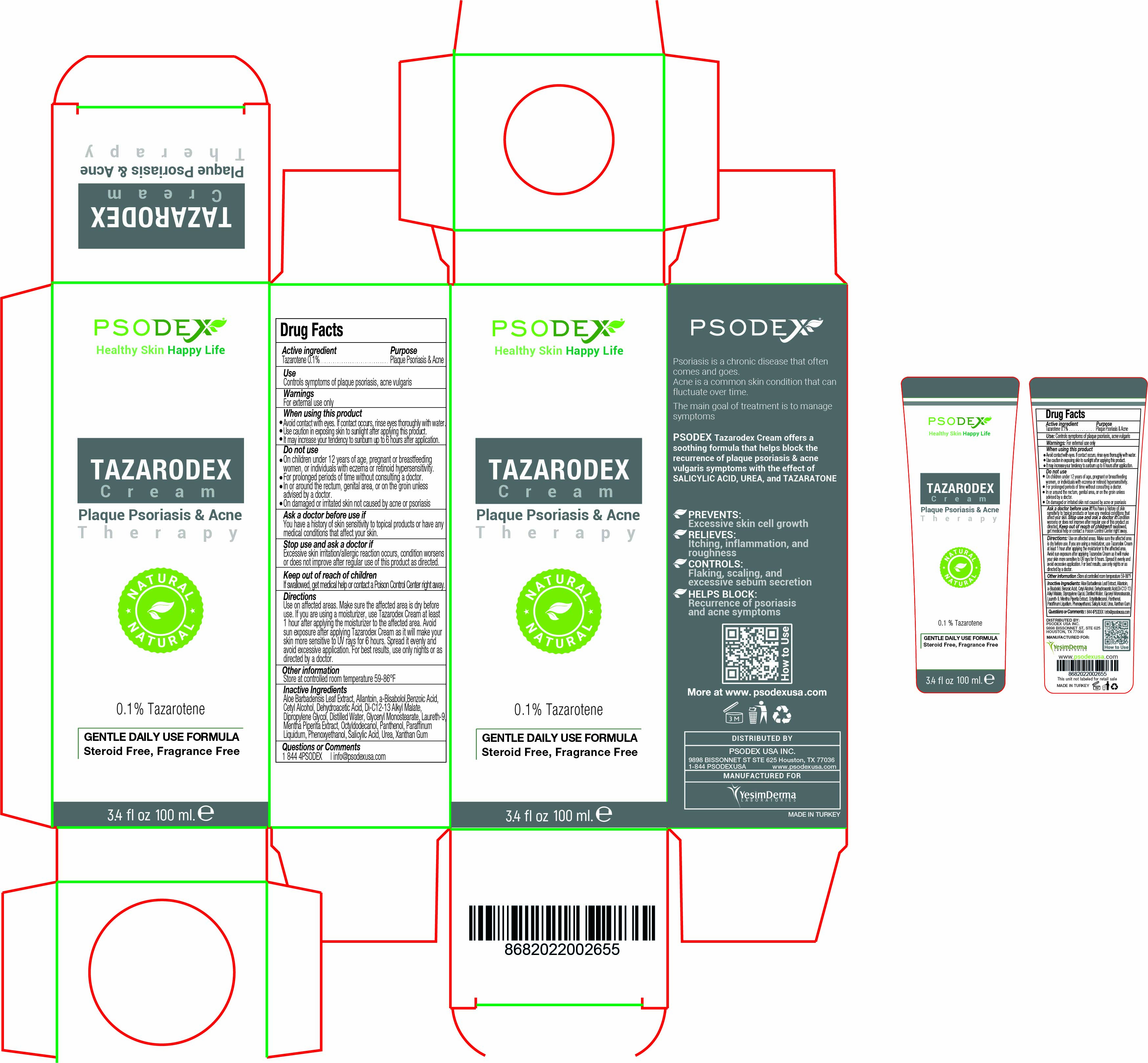 DRUG LABEL: Tazarodex
NDC: 73503-007 | Form: CREAM
Manufacturer: PSODEX USA INC
Category: otc | Type: HUMAN OTC DRUG LABEL
Date: 20231221

ACTIVE INGREDIENTS: TAZAROTENE 0.1 g/100 mL
INACTIVE INGREDIENTS: SALICYLIC ACID 1 g/100 mL; DEHYDROACETIC ACID 0.25 g/100 mL; DI-C12-13 ALKYL MALATE 2 g/100 mL; MINERAL OIL 5 g/100 mL; CETYL ALCOHOL 5 g/100 mL; XANTHAN GUM 0.3 g/100 mL; ALLANTOIN 2 g/100 mL; POLIDOCANOL 3 g/100 mL; MENTHA PIPERITA LEAF 5 g/100 mL; DIPROPYLENE GLYCOL 0.2 g/100 mL; GLYCERYL MONOSTEARATE 2 g/100 mL; PANTHENOL 1 g/100 mL; BENZOIC ACID 0.25 g/100 mL; OCTYLDODECANOL 2 g/100 mL; PHENOXYETHANOL 0.5 g/100 mL; UREA 5 g/100 mL; LEVOMENOL 2 g/100 mL

Tazarodex Cream Plaque Psoriasis & Acne

Tazarodex Cream Plaque Psoriasis & Acne

Psoriasis is a chronic disease that often comes and goes.

Acne is a common skin condition that can fluctuate over time.

The main goal of treatment is to manage symptoms.

PSODEX Tazarodex Cream offers a soothing formula that helps block the recurrence of plaque psoriasis & acne vulgaris symptoms with the effect of SALICYLIC ACID, UREA, and TAZARATONE.

The main goal of treatment is to manage symptoms.

PREVENTS:
Excessive skin cell growth

RELIEVES:
Itching, inflammation, and roughness

CONTROLS:

Flaking, scaling, and excessive sebum secretion

HELPS BLOCK:
Recurrence of psoriasis and acne symptoms

Tazarodex Cream Plaque Psoriasis & Acne

Inactive Ingredients:

Aloe Barbadensis Leaf Extract, Allantoin, a-Bisabolol,Benzoic Acid, Cetyl Alcohol, Dehydroacetic Acid, Di-C12-13 Alkyl Malate, Dipropylene Glycol, Distilled Water, Glyceryl Monostearate, Laureth-9, Mentha Piperita Extract, Octyldodecanol, Panthenol, Paraffinum Liquidum, Phenoxyethanol, Salicylic Acid, Urea, Xanthan Gum

Tazarodex Cream Plaque Psoriasis & Acne

Use:

Controls symptoms of plaque psoriasis, acne vulgaris

Tazarodex Cream Plaque Psoriasis & Acne

DISTRIBUTED BY: Psodex USA Inc.

9898 Bissonnet St Ste 625 Houston, TX 77036

1-844 4PSODEX www.psodexusa.com

MANUFACTURED FOR

Yesim Derma Laboratories

Tazarodex Cream Plaque Psoriasis & Acne - Directions

Directions:

Use on affected areas. Make sure the affected area is dry before use. If you are using a moisturizer, use Tazarodex Cream at least
1 hour after applying the moisturizer to the affected area. Avoid sun exposure after applying Tazarodex Cream as it will make your
skin more sensitive to UV rays for 6 hours. Spread it evenly and avoid excessive application. For best results, use only nights or as
directed by a doctor.

Tazarodex Cream Plaque Psoriasis & Acne

Active ingredient:

Tazarotene 0.1%

Tazarodex Cream Plaque Psoriasis & Acne

Ask a doctor before use if

You have a history of skin sensitivity to topical products or have any medical conditions that affect your skin.

Tazarodex Cream Plaque Psoriasis & Acne

Do not use:

- On children under 12 years of age, pregnant or breastfeeding women, or individuals with eczema or retinoid hypersensitivity.
- For prolonged periods of time without consulting a doctor.
- In or around the rectum, genital area, or on the groin unless advised by a doctor.
- On damaged or irritated skin not caused by acne or psoriasis

Tazarodex Cream Plaque Psoriasis & Acne

Keep out of reach of children: If swallowed, get medical help or contact a Poison Control Center right away.

Tazarodex Cream Plaque Psoriasis & Acne

Purpose:

Plaque Psoriasis & Acne

Tazarodex Cream Plaque Psoriasis & Acne

Questions or Comments: 1 844 4PSODEX | info@psodexusa.com

Tazarodex Cream Plaque Psoriasis & Acne

Stop use and ask a doctor if

Excessive skin irritation/allergic reaction occurs, condition worsens or does not improve after regular use of this product as directed.

Tazarodex Cream Plaque Psoriasis & Acne

When using this product:

- Avoid contact with eyes. If contact occurs, rinse eyes thoroughly with water.
- Use caution in exposing skin to sunlight after applying this product.
- It may increase your tendency to sunburn up to 6 hours after application.

Tazarodex Cream Plaque Psoriasis & Acne

Other information:

Store at controlled room temperature 59-86°F

Tazarodex Cream Plaque Psoriasis & Acne

Warnings: For external use only

Tazarodex Cream Plaque Psoriasis & Acne

Tazarotene 0.1%